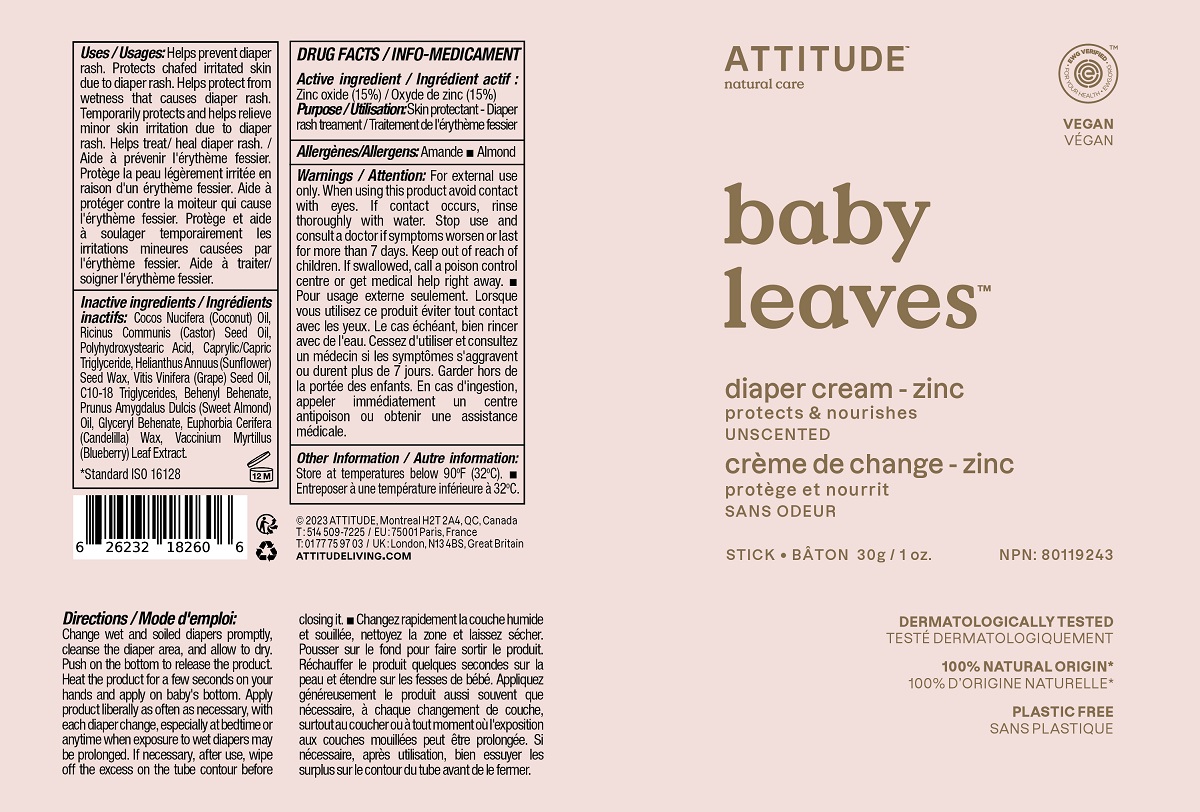 DRUG LABEL: Attitude Diaper Cream Zinc Unscented
NDC: 61649-260 | Form: STICK
Manufacturer: 9055-7588 Quebec Inc. (Attitude)
Category: otc | Type: HUMAN OTC DRUG LABEL
Date: 20241002

ACTIVE INGREDIENTS: ZINC OXIDE 15 g/100 g
INACTIVE INGREDIENTS: MEDIUM-CHAIN TRIGLYCERIDES; GLYCERYL MONOBEHENATE; CANDELILLA WAX; GRAPE SEED OIL; BEHENYL BEHENATE; ALMOND OIL; COCONUT OIL; CASTOR OIL; POLYHYDROXYSTEARIC ACID (2300 MW); HELIANTHUS ANNUUS SEED WAX; C10-18 TRIGLYCERIDES; VACCINIUM MYRTILLUS LEAF

ATTITUDE Baby Leaves Diaper Cream - Zinc - Unscented

DRUG FACTS

ACTIVE INGREDIENT

Zinc oxide (15%)

PURPOSE

Skin protectant - Diaper rash treatment

INDICATIONS AND USAGE

Helps prevent diaper rash.

Protects chafed irritated skin due to diaper rash.

Helps protect from wetness that causes diaper rash.

Temporarily protects and helps relieve minor skin irritation due to diaper rash.

Helps treat/heal diaper rash.

WARNINGS

Allergens: almond

For external use only.

When using this product avoid contact with eyes. If contact occurs, rinse thoroughly with water.

Stop use and consult a doctor if symptoms worsen or last for more than 7 days.

Keep out of reach of children. If swallowed, call a poison control centre or get edical help right away.

DOSAGE AND ADMINISTRATION

Change wet and soiled diapers promptly, cleanser the diaper area, and allow to dry. Push on the bottom to release the product. Heat the product for a few seconds on your hands and apply on baby's bottom. Apply product liberally as often as necessary, with each diaper change, especially at bedtime or anytime when exposure to wet diapers may be prolonged. If necessary, after use, wipe off the excess on the tube contour before closing it.

STORAGE AND HANDLING

Store at temperatures below 90 F (32 C).

INACTIVE INGREDIENT

Cocos Nucifera (Coconut) Oil, Ricinus Communis (Castor) Seed Oil, Polyhydroxystearic Acid, Caprylic/Capric Triglyceride, Helianthus Annuus (Sunflower) Seed Wax, Vitis Vinifera (Grape) Seed Oil, C10-18 Triglycerides, Behenyl Behenate, Prunus Amygdalus Dulcis (Sweet Almond) Oil, Glyceryl Behenate, Euphorbia Cerifera (Candelilla) Wax, Vaccinium Myrtillus (Blueberry) Leaf Extract.

PACKAGE LABEL

ATTITUDETM

natural care

baby leavesTM

diaper cream - zinc

protects & nourishes

Unscented

EWG VerifiedTM

Vegan

Stick 30g /1 oz.

NPN 80119243

dermatologically tested

plastic free